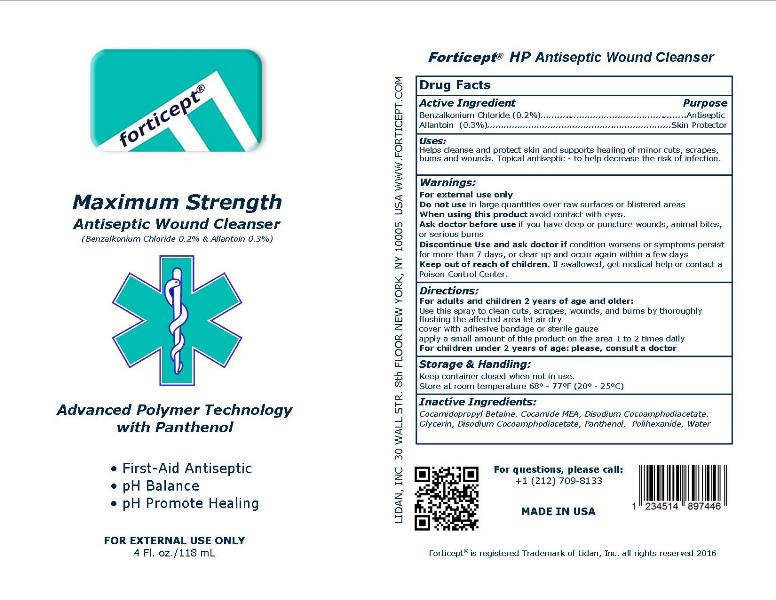 DRUG LABEL: Forticept HP Antiseptic Wound Cleanser
NDC: 72127-0807 | Form: SPRAY
Manufacturer: Lidan, inc.
Category: otc | Type: HUMAN OTC DRUG LABEL
Date: 20250325

ACTIVE INGREDIENTS: BENZALKONIUM CHLORIDE 0.002 kg/1 kg; ALLANTOIN 0.003 kg/1 kg
INACTIVE INGREDIENTS: COCO MONOETHANOLAMIDE; COCAMIDOPROPYL BETAINE; DISODIUM COCOAMPHODIACETATE; GLYCERIN; PANTHENOL; POLIHEXANIDE; WATER

Forticept HP Antiseptic Wound Cleanser

DRUG FACTS

Active Ingredient/Purpose

BENZALKONIUM CHLORIDE - 0.2% (ANTISEPTIC)
ALLANTOIN – 0.3% (SKIN PROTECTAN)

Uses:

Helps cleanse and protect skin and supports healing of minor cuts, scrapes, bums and wounds. Topical antiseptic - to help decrease the risk of infection.

INDICATIONS AND USAGE

Topical antiseptic - to help decrease the risk of wounf and skin infections.

WARNINGS:

For external use only!

Keep out of reach of children. If swallowed, get medical help or contact a Poison Control Center immidiately

Do not use
• in large quantities, particularly over raw surfaces or blistered areas

Ask doctor before use if you have
• deep or puncture wounds
• animal bites
• serious burns

When using this product
• avoid contact with eyes

Stop use and ask doctor if
• condition worsens
• symptoms persist for more than 7 days or clear up and occur again within a few days

Directions:

Adults and children 2 years of age and older:
• use the spray to clean cuts, scrapes, wounds and burns by thoroughly flushing the affected area
• let air dry
• cover with adhesive bandage or sterile gauze
• apply a small amount of this product on the area 1 to 2 times daily

Inactive Ingredients:

COCAMIDE MEA, COCAMIDOPROPYL BETAINE, DISODIUM COCOAMPHODIACETATE, GLYCERIN, PANTHENOL, POLIHEXANIDE, WATER

Storage and handling:

Keep container closed when not in use.
Store at room temperature 68° - 77°F (20° - 25°C)

For Questions:

Please call: +1 212 709-8133
Lidan, Inc.
30 Wall Street, 8th Floor
New York, NY 10005
www.forticept.com